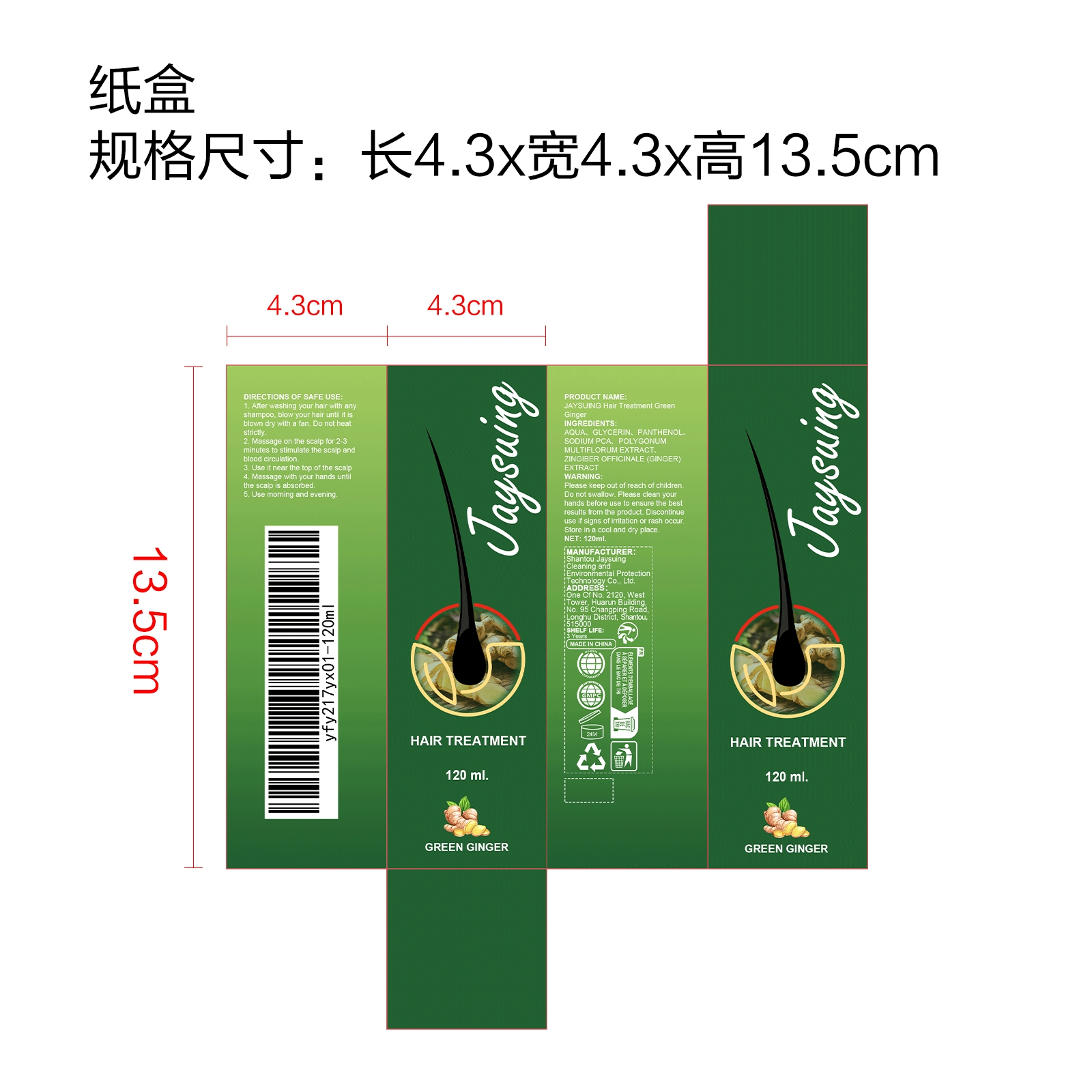 DRUG LABEL: JAYSUING Hair Treatment Green Ginger
NDC: 85060-002 | Form: LIQUID
Manufacturer: Shantou Jaysuing Cleaning and Environmental Protection Technology Co., Ltd.
Category: otc | Type: HUMAN OTC DRUG LABEL
Date: 20251127

ACTIVE INGREDIENTS: REYNOUTRIA MULTIFLORA ROOT 0.024 mg/120 mg; GINGER OIL 0.024 mg/120 mg
INACTIVE INGREDIENTS: SODIUM PCA 1.2 mg/120 mg; PANTHENOL 1.8 mg/120 mg; AQUA 112.152 mg/120 mg; GLYCERIN 4.8 mg/120 mg

ACTIVE INGREDIENTS

REYNOUTRIA MULTIFLORA ROOT、GINGER OIL

PURPOSE

Grow hair roots willfully and promote hair growth

USES

1. After washing your hair with any shampoo, blow your hair until it is blown dry with a fan. Do not heat strictly.

2. Massage on the scalp for 2-3 minutes to stimulate the scalp and blood circulation.

3. Use it near the top of the scalp

4. Massage with your hands until the scalp is absorbed.

5. Use moming and evening

Warnings

Please keep out of reach of children. Do not swallow. Please clean your hands before use to ensure the best results from the product. Discontinue use if signs of irritation or rash occur. Store in a cool and dry place.

Stop use

Discontinue use if signs of irritation or rash occur.

Do not use

Discontinue use if signs of irritation or rash occur.

KEEP OUT OF REACH OF CHILDREN

Please keep out of reach of children. Do not swallow.

STORAGE AND HANDLING

Store in a cool and dry place.

INACTIVE INGREDIENT

AQUA,
GLYCERIN,
PANTHENOL
SODIUM PCA